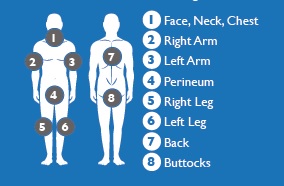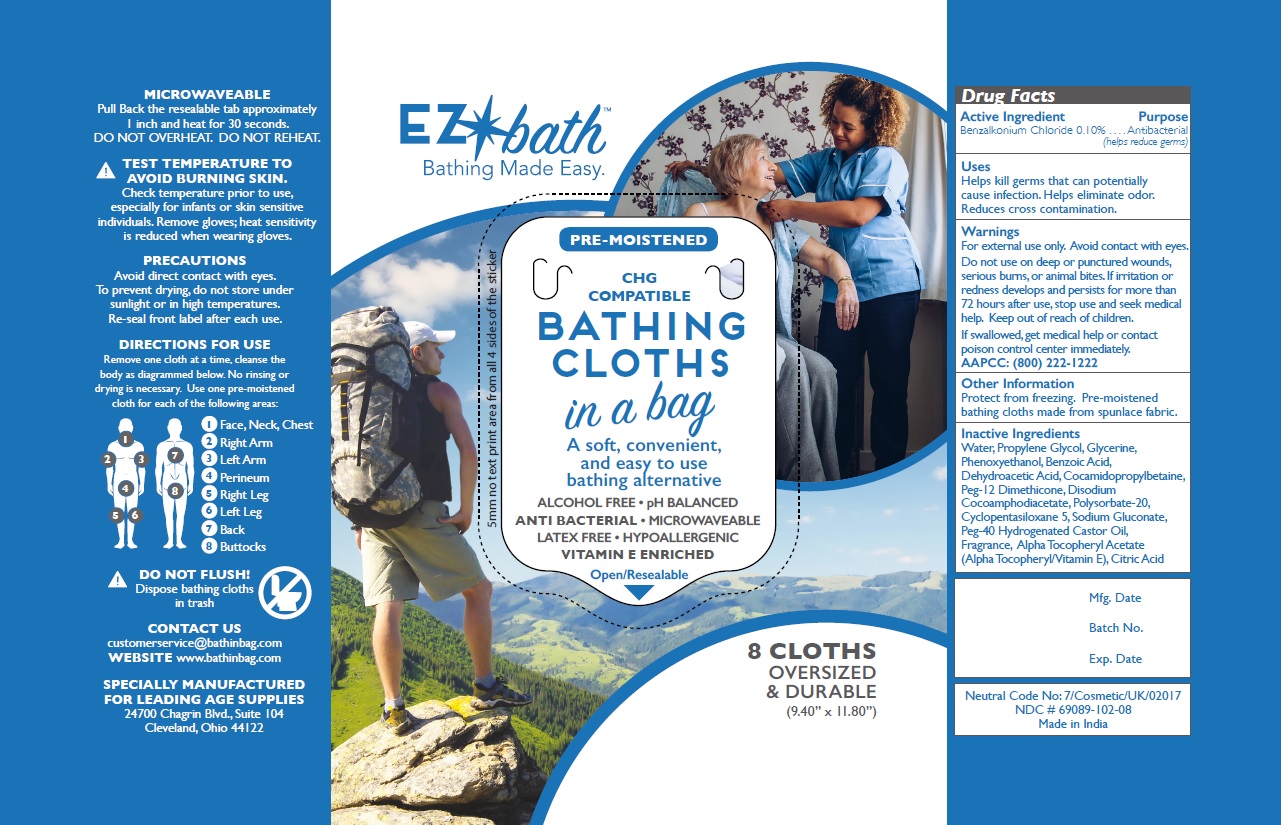 DRUG LABEL: PRE-MOISTENED BATHING CLOTHS
NDC: 69088-102 | Form: CLOTH
Manufacturer: Leading Age Supplies
Category: otc | Type: HUMAN OTC DRUG LABEL
Date: 20191106

ACTIVE INGREDIENTS: BENZALKONIUM CHLORIDE 0.143 g/1 1
INACTIVE INGREDIENTS: WATER; PROPYLENE GLYCOL; GLYCERIN; PHENOXYETHANOL; BENZOIC ACID; DEHYDROACETIC ACID; COCAMIDOPROPYL BETAINE; PEG-12 DIMETHICONE (300 CST); DISODIUM COCOAMPHODIACETATE; POLYSORBATE 20; CYCLOMETHICONE 5; SODIUM GLUCONATE; POLYOXYL 40 HYDROGENATED CASTOR OIL; .ALPHA.-TOCOPHEROL ACETATE; CITRIC ACID MONOHYDRATE

PRE-MOISTENED BATHING CLOTHS

Active Ingredient

Benzalkonium Chloride 0.10%

Purpose

Antibacterial

(helps reduce germs)

Uses

Helps kill germs that can potentially cause infection.

Helps eliminate odor.

Reduces cross contamination.

Warnings

For external use only.

Avoid contact with eyes.

Do not use on deep or punctured wounds, serious burns or animal bites. If irritation or redness develops, and persists for more than 72 hours after use, stop use and seek medical help.

Keep out of reach of children.

If swallowed, get medical help or contact poison control center immediately.
AAPCC: (800) 222-1222

DIRECTIONS FOR USE

Remove one cloth at a time, cleanse the body as diagrammed below. No rinsing or drying is necessary. Use one pre-moistened
cloth for each of the following areas:

DO NOT FLUSH! Dispose bathing cloths in trash

Other Information

Protect from freezing. Pre-moistened bathing cloths made from spunlace fabric.

Inactive Ingredients

Water, Propylene Glycol, Glycerine, Phenoxyethanol, Benzoic Acid, Dehydroacetic Acid, Cocamidopropylbetaine, Peg-12 Dimethicone, Disodium
Cocoamphodiacetate, Polysorbate-20, Cyclopentasiloxane 5, Sodium Gluconate, Peg-40 Hydrogenated Castor Oil, Fragrance, Alpha Tocopheryl Acetate (Alpha Tocopheryl/Vitamin E), Citric Acid.

A soft, convenient, and easy to use bathing alternative

ALCOHOL FREE • pH BALANCED
ANTI BACTERIAL • MICROWAVEABLE
LATEX FREE • HYPOALLERGENIC
VITAMIN E ENRICHED

CHG COMPATIBLE

Healthcare Facilities - Home Care Hikers - Cyclists - Campers - Truckers

MICROWAVEABLE
Pull Back the resealable tab approximately 1 inch and heat for 30 seconds.
DO NOT OVERHEAT. DO NOT REHEAT.

TEST TEMPERATURE TO AVOID BURNING SKIN.
Check temperature prior to use, especially for infants or skin sensitive individuals.
Remove gloves; heat sensitivity is reduced when wearing gloves.

PRECAUTIONS
Avoid direct contact with eyes. To prevent drying, do not store under sunlight or in high temperatures.
Re-seal front label after each use.

SPECIALLY MANUFACTURED
FOR LEADING AGE SUPPLIES
24700 Chagrin Blvd., Suite 104
Cleveland, Ohio 44122
www.bathinbag.com